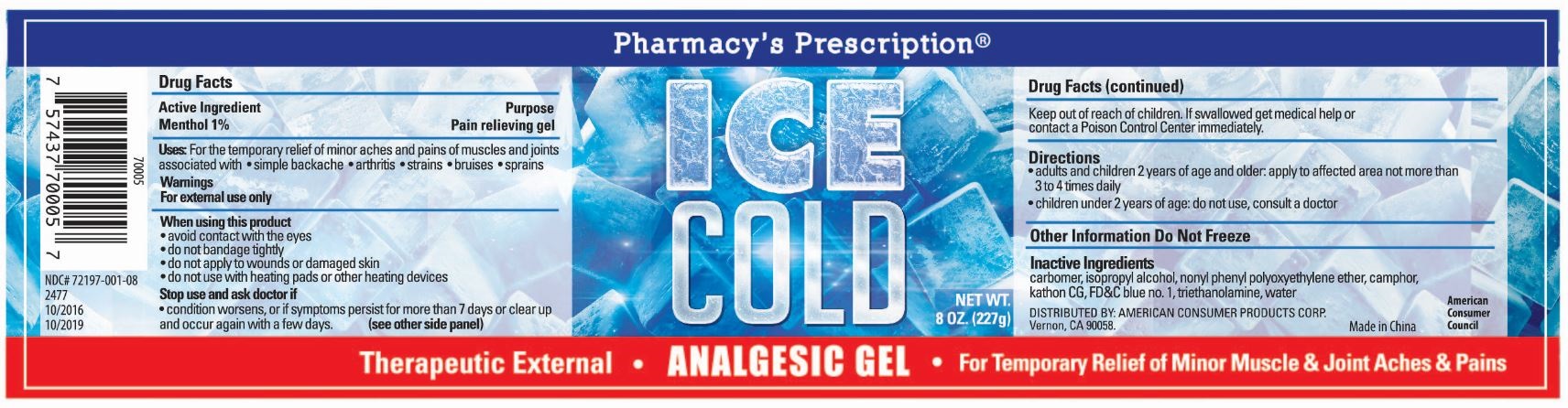 DRUG LABEL: Pharmacys Prescription Analgesic Gel
NDC: 72197-001 | Form: GEL
Manufacturer: American Consumer Products Corp
Category: otc | Type: HUMAN OTC DRUG LABEL
Date: 20250123

ACTIVE INGREDIENTS: MENTHOL 1 g/100 g
INACTIVE INGREDIENTS: ISOPROPYL ALCOHOL; CAMPHOR, (-)-; CARBOMER 940; METHYLCHLOROISOTHIAZOLINONE/METHYLISOTHIAZOLINONE MIXTURE; 2,2',3,3',4,4',5,5',6-NONACHLORODIPHENYL ETHER; TRIETHANOLAMINE LAURYL SULFATE; WATER

Pharmacy's Prescription 8OZ Ice Cold Analgesic Gel

Active Ingredient

Active Ingredient: Menthol 1%

Purpose

Purpose: Pain relieving gel

Warnings

Warnings: For external use only

Stop Use

Stop use and ask doctor if

- condition worsens, or if symptoms persist for more than 7 days or clear up and occur again within a few days.

Keep out of reach of children

Keep our of reach of children. If swallowed get medical help or contact a Poison Control Center immediately.

Inactive Ingredients

carbomer, isopropyl alcohol, nonyl phenyl polyoxyethylene ether, camphor, kathon CG, FD&C blue no. 1, triethanolamine, water

Indications & Usage Section

Uses: For the temporary relief of minor aches and pains of muscles and joints associated with - simple backache - arthritis - strains - bruses - sprains

When using this product

- avoid contact with eyes

- do not bandage tightly

- do not apply to wounds or damaged skin

- do not use with heating pads or other heating devices

Dosage & Administration

Directions

- adults and childrent 2 years of age and older: apply to affected area not more than 3 to 4 times daily

- children under 2 years of age: do not use, consult a doctor